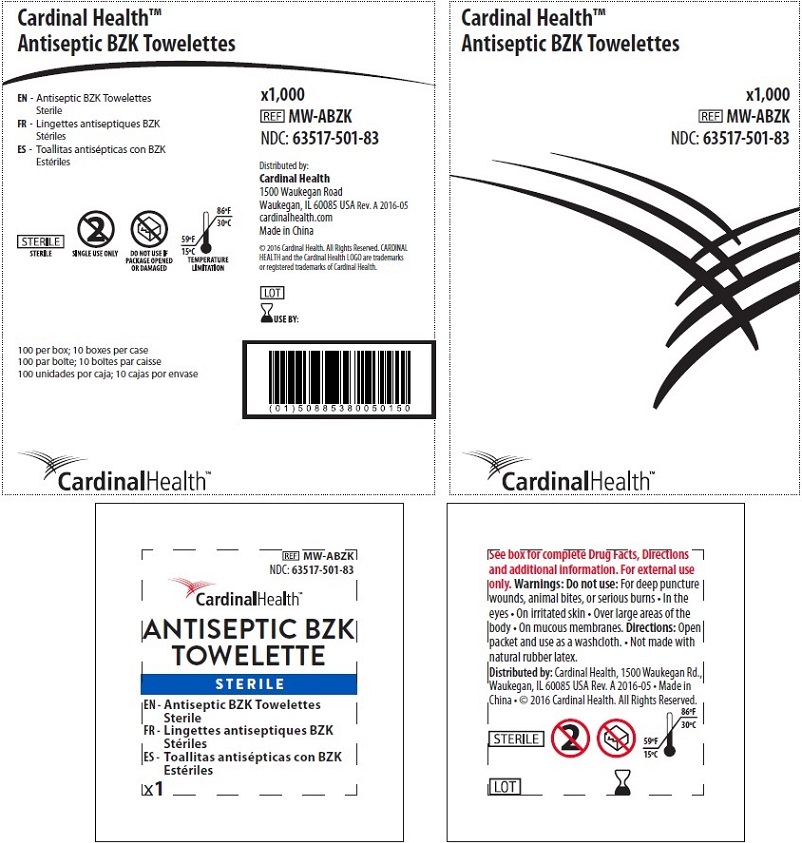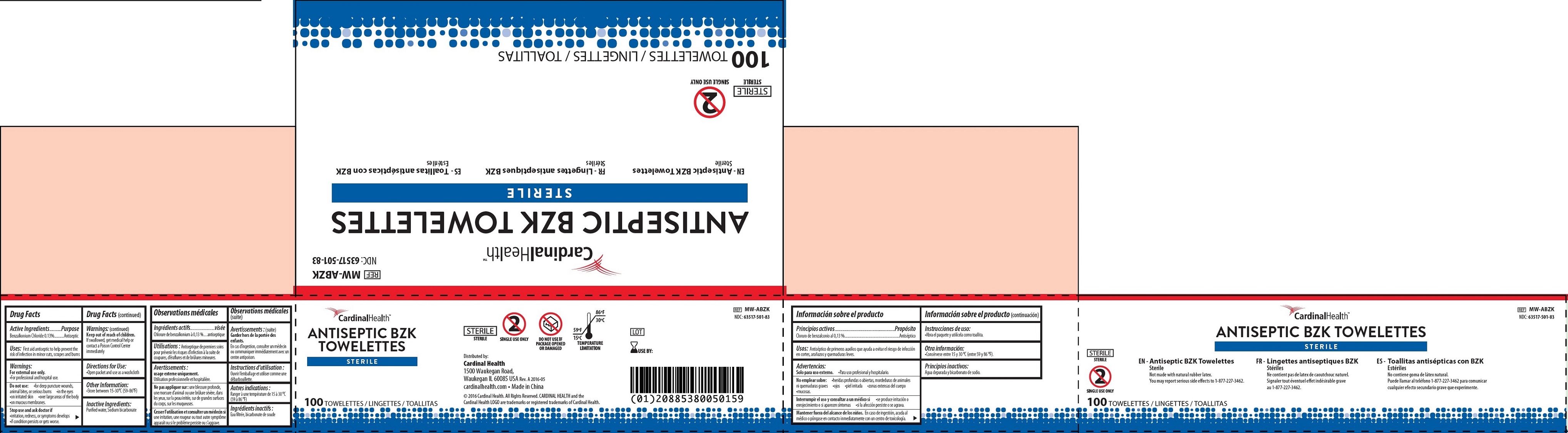 DRUG LABEL: Antiseptic BZK Towelette
NDC: 63517-501 | Form: CLOTH
Manufacturer: Cardinal Health 200, Inc.
Category: otc | Type: HUMAN OTC DRUG LABEL
Date: 20231023

ACTIVE INGREDIENTS: BENZALKONIUM CHLORIDE 1.3 mg/1 g
INACTIVE INGREDIENTS: WATER; SODIUM BICARBONATE

Antiseptic BZK Towelette

Active Ingredients

Benzalkonium Chloride 0.13%

Purpose

Antiseptic

Uses:

First aid antiseptic to help prevent the risk of infection in minor cuts, scrapes and burns

Warnings:

• For professional and hospital use. For external use only.

Do not use:

• for deep puncture wounds, animal bites, or serious burns • in the eyes • on irritated skin • over large areas of the body • on mucous membranes.

Stop use and ask doctor if

•irritation, redness, or symptoms develops •if condition persists or gets worse.

Keep out of reach of children.

If swallowed, get medical help or contact a Poison Control Center Uses: First aid antiseptic to help prevent the immediately

Directions for Use:

• Open packet and use as a washcloth

Other Information:

•Store between 15-30°C (59-86°F)

Inactive Ingredients:

Purified water, Sodium bicarbonate